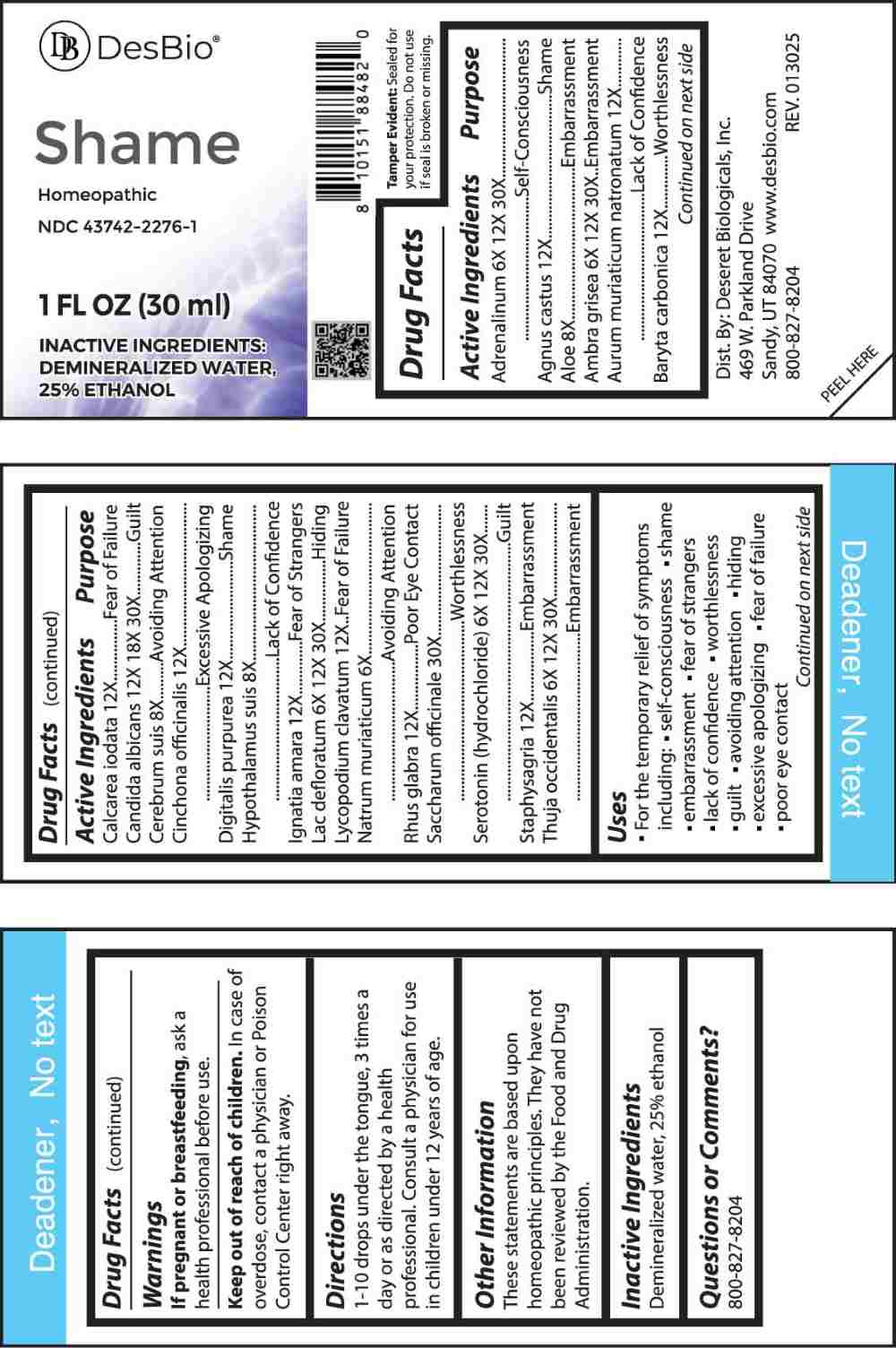 DRUG LABEL: Shame
NDC: 43742-2276 | Form: LIQUID
Manufacturer: Deseret Biologicals, Inc.
Category: homeopathic | Type: HUMAN OTC DRUG LABEL
Date: 20250507

ACTIVE INGREDIENTS: EPINEPHRINE 6 [hp_X]/1 mL; CHASTE TREE FRUIT 12 [hp_X]/1 mL; ALOE 8 [hp_X]/1 mL; AMBERGRIS 6 [hp_X]/1 mL; SODIUM TETRACHLOROAURATE 12 [hp_X]/1 mL; BARIUM CARBONATE 12 [hp_X]/1 mL; CALCIUM IODIDE 12 [hp_X]/1 mL; CANDIDA ALBICANS 12 [hp_X]/1 mL; SUS SCROFA CEREBRUM 8 [hp_X]/1 mL; CINCHONA OFFICINALIS BARK 12 [hp_X]/1 mL; DIGITALIS 12 [hp_X]/1 mL; SUS SCROFA HYPOTHALAMUS 8 [hp_X]/1 mL; STRYCHNOS IGNATII SEED 12 [hp_X]/1 mL; SKIM MILK 6 [hp_X]/1 mL; LYCOPODIUM CLAVATUM SPORE 12 [hp_X]/1 mL; SODIUM CHLORIDE 6 [hp_X]/1 mL; RHUS GLABRA TOP 12 [hp_X]/1 mL; SUCROSE 30 [hp_X]/1 mL; SEROTONIN HYDROCHLORIDE 6 [hp_X]/1 mL; DELPHINIUM STAPHISAGRIA SEED 12 [hp_X]/1 mL; THUJA OCCIDENTALIS LEAFY TWIG 6 [hp_X]/1 mL
INACTIVE INGREDIENTS: WATER; ALCOHOL

DRUG FACTS:

ACTIVE INGREDIENTS:

Adrenalinum 6X, 12X, 30X, Agnus Castus 12X, Aloe 8X, Ambra Grisea 6X, 12X, 30X, Aurum Muriaticum Natronatum 12X, Baryta Carbonica 12X, Calcarea Iodata 12X, Candida Albicans 12X, 18X, 30X, Cerebrum Suis 8X, Cinchona Officinalis 12X, Digitalis Purpurea 12X, Hypothalamus Suis 8X, Ignatia Amara 12X, Lac Defloratum 6X, 12X, 30X, Lycopodium Clavatum 12X, Natrum Muriaticum 6X, Rhus Glabra 12X, Saccharum Officinale 30X, Serotonin (Hydrochloride) 6X, 12X, 30X, Staphysagria 12X, Thuja Occidentalis 6X, 12X, 30X.

PURPOSE:

Adrenalinum – Self-Consciousness, Agnus Castus - Shame, Aloe - Embarrassment, Ambra Grisea - Embarrassment, Aurum Muriaticum Natronatum – Lack of Confidence, Baryta Carbonica - Worthlessness, Calcarea Iodata – Fear of Failure, Candida Albicans - Guilt, Cerebrum Suis – Avoiding Attention, Cinchona Officinalis – Excessive Apologizing, Digitalis Purpurea - Shame, Hypothalamus Suis – Lack of Confidence, Ignatia Amara – Fear of Strangers, Lac Defloratum - Hiding, Lycopodium Clavatum – Fear of Failure, Natrum Muriaticum – Avoiding Attention, Rhus Glabra – Poor Eye Contact, Saccharum Officinale - Worthlessness, Serotonin (Hydrochloride) - Guilt, Staphysagria - Embarrassment, Thuja Occidentalis - Embarrassment

USES:

• For the temporary relief of symptoms including:
• self-consciousness • shame • embarrassment • fear of strangers • lack of confidence • worthlessness

•guilt • avoiding attention • hiding • excessive apologizing • fear of failure • poor eye contact

These statements are based upon homeopathic principles. They have not been reviewed by the Food and Drug Administration.

WARNINGS:

If pregnant or breastfeeding, ask a health professional before use.

Keep out of reach of children. In case of overdose, contact a physician or Poison Control Center right away.

Tamper Evident: Sealed for your protection. Do not use if seal is broken or missing.

KEEP OUT OF REACH OF CHILDREN:

In case of overdose, contact a physician or Poison Control Center right away.

DIRECTIONS:

1-10 drops under the tongue, 3 times a day or as directed by a health professional. Consult a physician for use in children under 12 years of age.

INACTIVE INGREDIENTS:

Demineralized water, 25% ethanol

QUESTIONS:

Dist. By: Deseret Biologicals, Inc.

469 W. Parkland Drive

Sandy, UT 84070

www.desbio.co

800-827-8204

PACKAGE LABEL DISPLAY:

Shame

Homeopathic

NDC 43742-2276-1

1 FL OZ (30 ml)